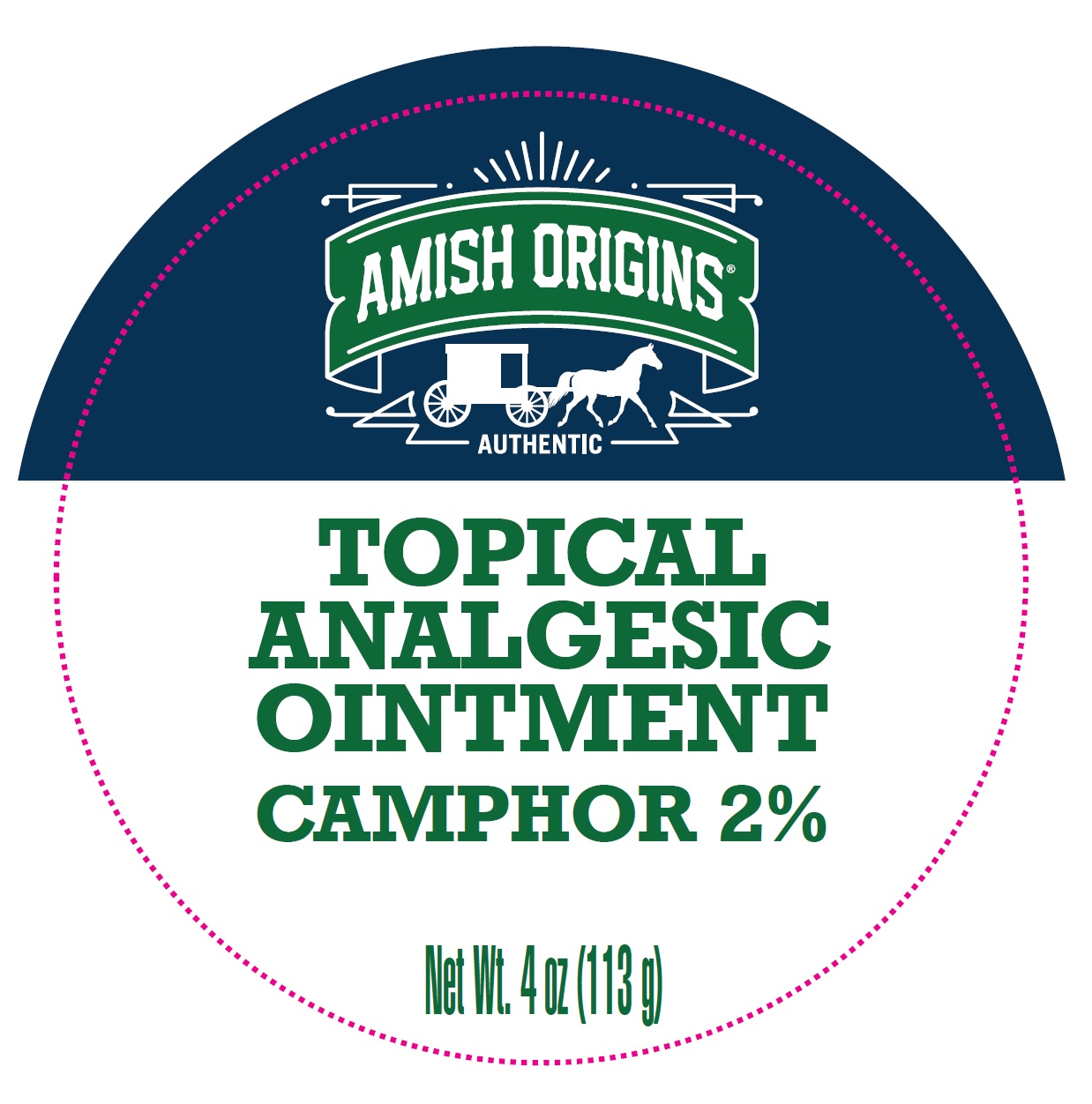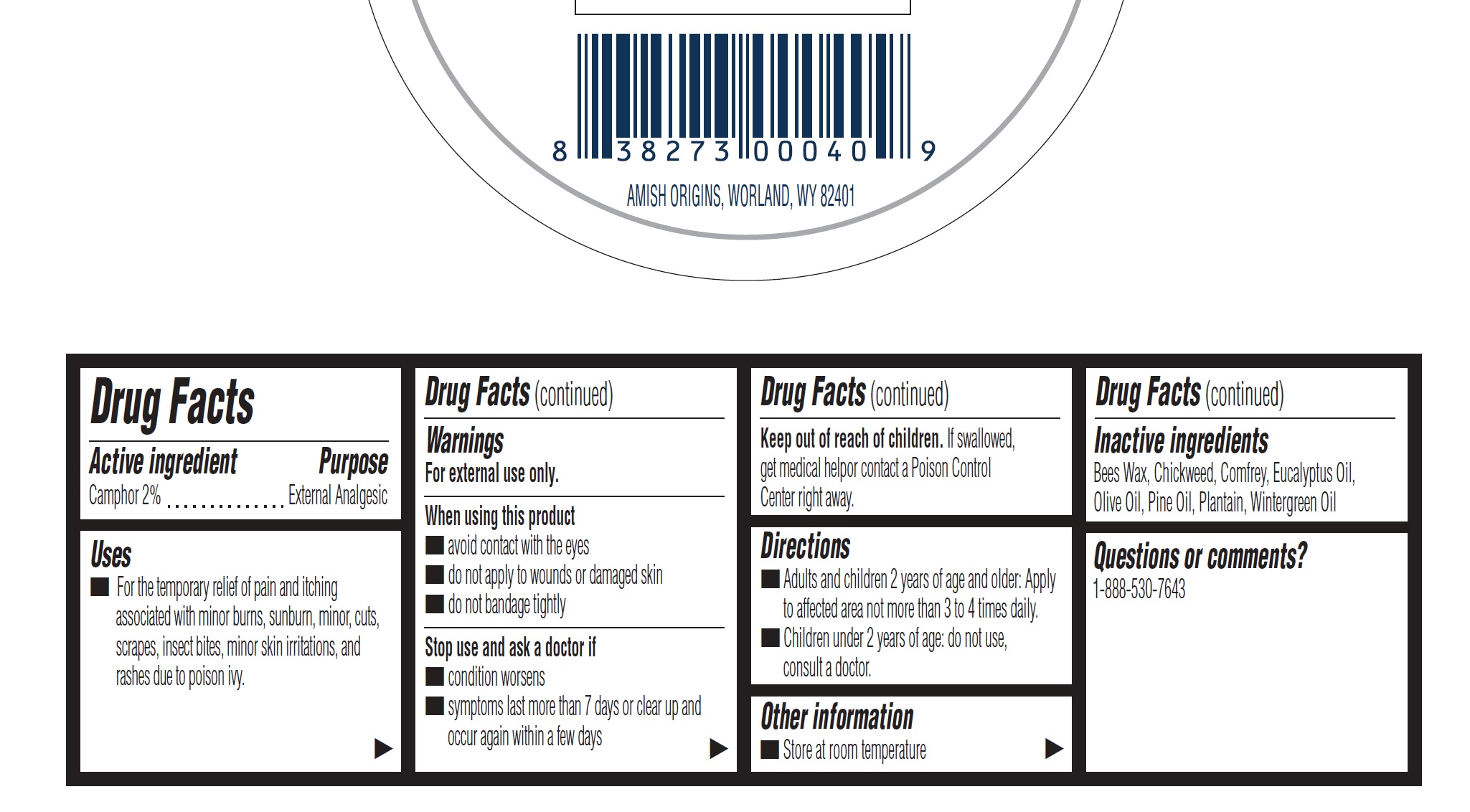 DRUG LABEL: Amish Origins Topical Analgesic Camphor 2%
NDC: 62212-004 | Form: SALVE
Manufacturer: Amish Origins Management, LLC
Category: otc | Type: HUMAN OTC DRUG LABEL
Date: 20240229

ACTIVE INGREDIENTS: CAMPHOR (SYNTHETIC) 20 mg/1 g
INACTIVE INGREDIENTS: YELLOW WAX; STELLARIA MEDIA; SYMPHYTUM X UPLANDICUM LEAF; EUCALYPTUS OIL; OLIVE OIL; WHITE PINE OIL; METHYL SALICYLATE

Amish Origins Topical Analgesic Ointment Camphor 2%

Active ingredient

Camphor 2%

Purpose

External Analgesic

Uses

- For the temporary relief of pain and itching associated with minor burns, sunburn, minor, cuts, scrapes, insect bites, minor skin irritations, and rashes due to poison ivy.

Warnings

For external use only.

When using this product

- avoid contact with the eyes
- do not apply to wounds or damaged skin
- do not bandage tightly

Stop use and ask a doctor if

- condition worsens
- symptoms last more than 7 days or clear up and occur again within a few days

Keep out of reach of children.

If swallowed, get medical helpor contact a Poison Control Center right away.

Directions

- Adults and children 2 years of age and older: Apply to affected area not more than 3 to 4 times daily.
- Children under 2 years of age: do not use, consult a doctor.

Other information

- Store at room temperature

Inactive ingredients

Bees Wax, Chickweed, Comfrey, Eucalyptus Oil, Olive Oil, Pine Oil, Plantain, Wintergreen Oil

Questions or comments?

1-888-530-7643